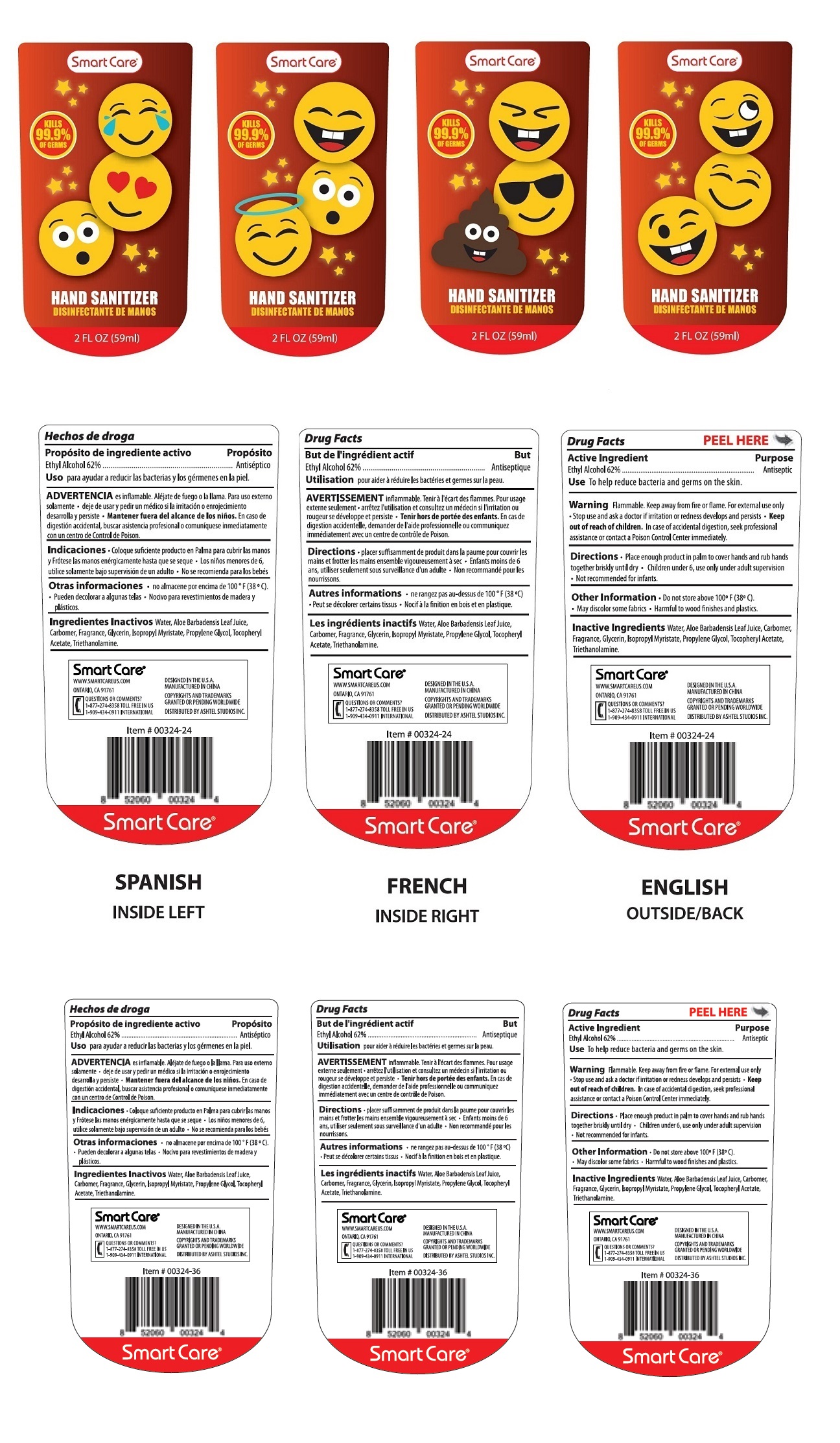 DRUG LABEL: Smart Care Generic Emoji Hand Sanitizer
NDC: 70108-011 | Form: LIQUID
Manufacturer: Ashtel Studios, Inc.
Category: otc | Type: HUMAN OTC DRUG LABEL
Date: 20180216

ACTIVE INGREDIENTS: ALCOHOL 62 mL/100 mL
INACTIVE INGREDIENTS: WATER; ALOE VERA LEAF; CARBOXYPOLYMETHYLENE; GLYCERIN; ISOPROPYL MYRISTATE; PROPYLENE GLYCOL; .ALPHA.-TOCOPHEROL ACETATE; TROLAMINE

Smart Care Generic Emoji Hand Sanitizer

Active Ingredient

Ethyl Alcohol 62%

Purpose

Antiseptic

INDICATIONS AND USAGE

Use To help reduce bacteria and germs on the skin

WARNINGS

Warning Flammable. Keep away from fire or flame. For external use only • Stop use and ask a doctor if irritation or redness develops and persists

Keep out of reach of children. In case of accidental digestion, seek professional assistance or contact a Poison Control Center immediately.

DOSAGE AND ADMINISTRATION

Directions • Place enough product in palm to cover hands and rub hands together briskly until dry • Children under 6, use only under adult supervision • Not recommended for infants.

Other Information • Do not store above 100o F (38o C). • May discolor some fabrics • Harmful to wood finishes and plastics.

INACTIVE INGREDIENT

Inactive Ingredients Water, Aloe Barbadensis Leaf Juice, Carbomer, Fragrance, Glycerin, Isopropyl Myristate, Propylene Glycol, Tocopheryl Acetate, Triethanolamine.

Smart Care

WWW.SMARTCAREUS.COM

ONTARIO, CA 91761

QUESTIONS OR COMMENTS?

1-877-274-8358 TOLL FREE IN US

1-909-434-0911 INTERNATIONAL

DESIGNED IN THE U.S.A

MANUFACTURED IN CHINA

COPYRIGHTS AND TRADEMARKS

GRANTED OR PENDING WORLDWIDE

DISTRIBUTED BY ASHTEL STUDIOS INC